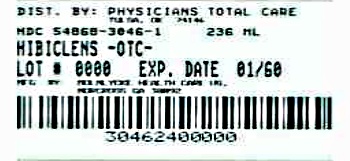 DRUG LABEL: Hibiclens
NDC: 54868-3046 | Form: SOLUTION
Manufacturer: Physicians Total Care, Inc.
Category: otc | Type: HUMAN OTC DRUG LABEL
Date: 20120919

ACTIVE INGREDIENTS: CHLORHEXIDINE GLUCONATE 213 g/1000 mL
INACTIVE INGREDIENTS: Isopropyl alcohol; FD&C Red NO. 40; Water

HIBICLENS®
(Chlorhexidine Gluconate
solution 4.0% w/v)

Drug Facts

ACTIVE INGREDIENT

Active ingredient | Purpose
Chlorhexidine gluconate solution 4.0% w/v | Antiseptic

Uses

- antimicrobial skin cleanser helps reduce bacteria that potentially can cause disease
- for skin wound and general skin cleansing
- surgical hand scrub
- personnel hand wash
- preoperative skin preparation

Warnings

For external use only

Do not use

- if you are allergic to chlorhexidine gluconate or any other ingredients in this preparation
- as a patient preoperative skin preparation of the head or face
- in contact with the meninges
- in the genital area
- on wounds that involve more than the superficial layers of skin

When using this product

- keep out of eyes, ears, and mouth. May cause serious and permanent eye injury if placed or kept in the eye during surgical procedures, or may cause deafness when instilled in the middle ear through perforated eardrums.
- if contact occurs in any of these areas, rinse with cold water right away

Stop use and ask a doctor if

- irritation, sensitization, or allergic reaction occurs and lasts for 72 hours.These may be signs of a serious condition.

Keep out of reach of children.

If swallowed, get medical help or contact a Poison Control Center right away.

Directions

- skin wound and general skin cleansing. Thoroughly rinse the area to be cleansed with water. Apply the minimum amount of HIBICLENS necessary to cover the skin or wound area and wash gently. Rinse thoroughly.
- surgical hand scrub. Wet hands and forearms with water. Scrub for 3 minutes with about 5mL of HIBICLENS with a brush. Rinse thoroughly under running water. Repeat. Dry thoroughly.
- personnel hand wash. Wet hands with water. Dispense about 5mL of HIBICLENS into cupped hands and wash in a vigorous manner for 15 seconds. Rinse and dry thoroughly.
- preoperative skin preparation. Apply HIBICLENS liberally to surgical site and swab for at least 2 minutes. Dry with a sterile towel. Repeat. Dry with a sterile towel.

Other information

store between 20-25°C (68-77°F).

Inactive ingredients

fragrance, isopropyl alcohol 4% w/v, purified water, Red 40, and other ingredients in a nonalkaline base.

Questions?

1-800-843-8497

PRINCIPAL DISPLAY PANEL - 236 mL Bottle Label

NDC 54868-3046-1

HIBICLENS®
(Chlorhexidine Gluconate
solution 4.0% w/v)

Antiseptic/Antimicrobial Skin Cleanser

HIBICLENS® prevents skin infections thereby reducing the risk of cross-
infection. HIBICLENS® has antiseptic activity and a persistent antimicrobial
effect with rapid bactericidal activity against a wide range of microorganisms.

MÖLNLYCKE®
HEALTH CARE

8 Fl. oz. (236 mL)

Distributed by Mölnlycke Health Care US, LLC
Norcross, GA 30092

Additional barcode labeling by:
Physicians Total Care, Inc.
Tulsa, Oklahoma 74146